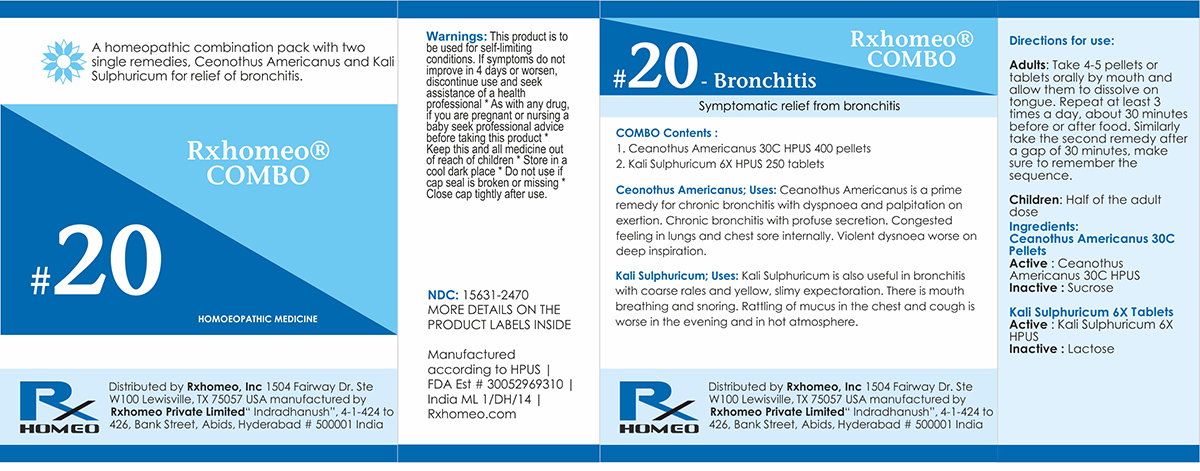 DRUG LABEL: Rxhomeo Homeopathic Combo 20
NDC: 15631-2470 | Form: KIT | Route: ORAL
Manufacturer: Rxhomeo Private Limited d.b.a.
Category: homeopathic | Type: HUMAN OTC DRUG LABEL
Date: 20161024

ACTIVE INGREDIENTS: CEANOTHUS AMERICANUS LEAF 1 [hp_X]/1 1; POTASSIUM SULFATE 1 [hp_X]/1 1
INACTIVE INGREDIENTS: SUCROSE; LACTOSE

ACTIVE INGREDIENT

CEANOTHUS AMERICANUS HPUS 1X and higher

KALI SULPHURICUM HPUS 1X and higher

USES

A homeopathic combination pack with two single remedies, Ceonothus Americanus and Kali Sulphuricum for relief of bronchitis.

Ceonothus Americanus: Ceanothus Americanus is a prime remedy for chronic bronchitis with dyspnoea and palpitation on exertion. Chronic bronchitis with profuse secretion. Congested feeling in lungs and chest sore internally. Violent dysnoea worse on deep inspiration.

Kali Sulphuricum: Kali Sulphuricum is also useful in bronchitis with coarse rales and yellow, slimy expectoration. There is mouth breathing and snoring. Rattling of mucus in the chest and cough is worse in the evening and in hot atmosphere.

INDICATIONS

Condition listed above or as directed by the physician

DOSAGE

Adults: Take 4-5 pellets or tablets orally by mouth and allow them to dissolve on tongue. Repeat at least 3 times a day, about 30 minutes before or after food. Similarly take the second remedy after a gap of 30 minutes, make sure to remember the sequence.

Children: Half of the adult dose.

WARNINGS

This product is to be used for self-limiting conditions

STOP USE

If symptoms do not improve in 4 days, or worsen, discontinue use and seek assistance of health professional

KEEP OUT OF REACH OF CHILDREN

Keep this and all medication out of reach of children

Do not use if capseal is broken or missing.

Close the cap tightly after use.

INACTIVE INGREDIENTS

Sucrose for Pellets.

Lactose for Tablets.

STORAGE

Store in a cool dark place

QUESTIONS OR COMMENTS

www.Rxhomeo.com | 1.888.2796642 | info@rxhomeo.com
Rxhomeo, Inc 1504 Fairway Dr. Ste W 100 Lewisville, TX 75057 USA